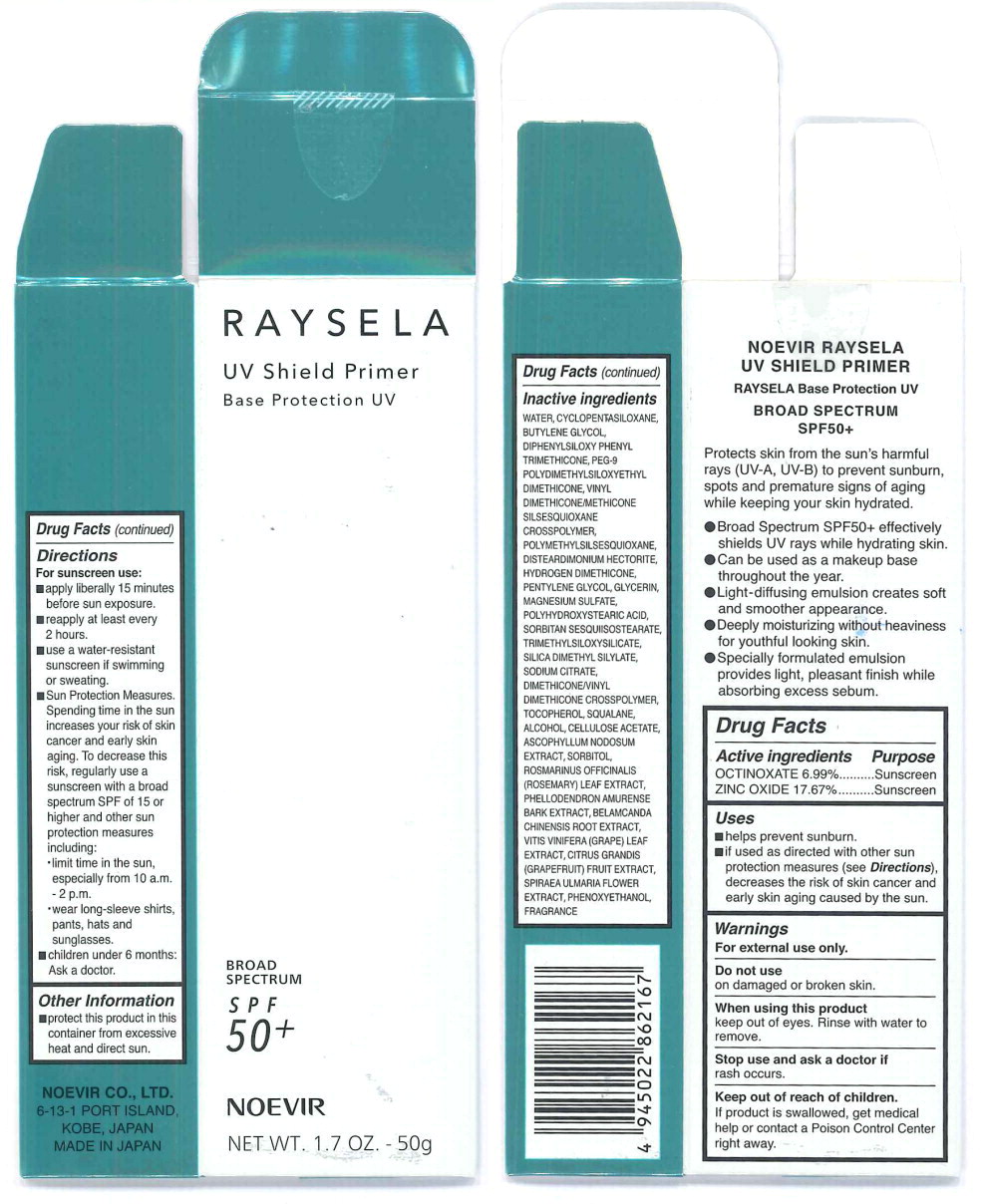 DRUG LABEL: Noevir Raysela UV Shield Primer
NDC: 24509-0001 | Form: CREAM
Manufacturer: Nippon Shikizai, Inc.
Category: otc | Type: HUMAN OTC DRUG LABEL
Date: 20250514

ACTIVE INGREDIENTS: ZINC OXIDE 176.7 mg/1 g; OCTINOXATE 69.9 mg/1 g
INACTIVE INGREDIENTS: WATER; CYCLOMETHICONE 5; BUTYLENE GLYCOL; DIPHENYLSILOXY PHENYL TRIMETHICONE; PEG-9 POLYDIMETHYLSILOXYETHYL DIMETHICONE; POLYMETHYLSILSESQUIOXANE (4.5 MICRONS); VINYL DIMETHICONE/METHICONE SILSESQUIOXANE CROSSPOLYMER; DISTEARDIMONIUM HECTORITE; HYDROGEN DIMETHICONE (13 CST); GLYCERIN; PENTYLENE GLYCOL; MAGNESIUM SULFATE, UNSPECIFIED FORM; PHENOXYETHANOL; POLYHYDROXYSTEARIC ACID (2300 MW); SORBITAN SESQUIISOSTEARATE; TRIMETHYLSILOXYSILICATE (M/Q 0.6-0.8); SILICA DIMETHYL SILYLATE; SODIUM CITRATE, UNSPECIFIED FORM; SQUALANE; TOCOPHEROL; CELLULOSE ACETATE; ROSEMARY; ALCOHOL; PHELLODENDRON AMURENSE BARK; PUMMELO; FILIPENDULA ULMARIA FLOWER; IRIS DOMESTICA ROOT; VITIS VINIFERA LEAF; ASCOPHYLLUM NODOSUM; SORBITOL; DIMETHICONE/VINYL DIMETHICONE CROSSPOLYMER (SOFT PARTICLE)

NOEVIR RAYSELA
UV SHIELD PRIMER
RAYSELA Base Protection UV
BROAD SPECTRUM
SPF50+

Protects skins from the sun's harmful rays (UV-A, UV-B) to prevent sunburn, spots and premature signs of aging while keeping your skin hydrated.

- Broad Spectrum SPF50+ effectively shields UV rays while hydrating skin.
- Can be used as a makeup base throughout the year.
- Light-diffusing emulsion creates soft and smoother appearance.
- Deeply moisturizing without heaviness for youthful looking skin.
- Specially formulated emulsion provided light, pleasant finish while absorbing excess sebum.

Drug Facts

Active Ingredients

OCTINOXATE 6.99%

ZINC OXIDE 17.67%

Purpose

Sunscreen

Sunscreen

Uses

- helps prevent sunburn.
- if used as directed with other sun protection measures (see Directions), decreases the risk of skin cancer and early skin aging caused by the sun.

Warnings

For external use only.

Do not use

on damaged or broken skin.

When using this product

keep out of eyes. Rinse with water to remove.

Stop use and ask a doctor if

rash occurs.

Keep out of reach of children.

If product is swallowed, get medical help or contact a Poison Control Center right away.

Directions

For sunscreen use:

- apply liberally 15 minutes before sun exposure.
- reapply at least every 2 hours.
- use a water-resistant sunscreen if swimming or sweating.
- Sun Protection Measures. Spending time in the sun increases your risk of skin cancer and early skin aging. To decrease this risk, regularly use a sunscreen with a broad spectrum SPF of 15 or higher and other sun protection measures including:
  - limit time in the sun, especially from 10 a.m. - 2 p.m
  - wear long-sleeve-shirts pants, hats and sunglasses.
- children under 6 months: Ask a doctor.

Other Information

- protect this product in this container from excessive heat and direct sun.

Inactive ingredients

WATER, CYCLOPENTASILOXANE, BUTYLENE GLYCOL, DIPHENYLSILOXY PHENYL TRIMETHICONE, PEG-9 POLYDIMETHYLSILOXYETHYL DIMETHICONE, VINYL DIMETHICONE/METHICONE SILSESQUIOXANE CROSSPOLYMER, POLYMETHYLSILSESQUIOXANE, DISTEARDIMONIUM HECTORITE, HYDROGEN DIMETHICONE, PENTYLENE GLYCOL, GLYCERIN, MAGNESIUM SULFATE, POLYHYDROXYSTEARIC ACID, SORBITAN SESQUIISOSTEARATE, TRIMETHYLSILOXYSILICATE, SILICA DIMETHYL SILYLATE, SODIUM CITRATE, DIMETHICONE/VINYL DIMETHICONE CROSSPOLYMER, TOCOPHEROL, SQUALANE, ALCOHOL, CELLULOSE ACETATE, ASCOPHYLLUM NODOSUM EXTRACT, SORBITOL, ROSMARINUS OFFICINALIS (ROSEMARY) LEAF EXTRACT, PHELLODENDRON AMURENSE BARK EXRACT, BELAMCANDA CHINENSIS ROOT EXTRACT, VITIS VINIFERA (GRAPE) LEAF EXTRACT, CITRUS GRANDIS (GRAPEFRUIT) FRUIT EXTRACT, SPIRAEA ULMARIA FLOWER EXTRACT, PHENOXYETHANOL, FRAGRANCE

Principal Display Panel - Raysela UV Shield Primer Label

RAYSELA

UV Shield Primer

Base Protection UV

BROAD
SPECTRUM

SPF
50+

NOEVIR

NET WT. 1.7 OZ. - 50g